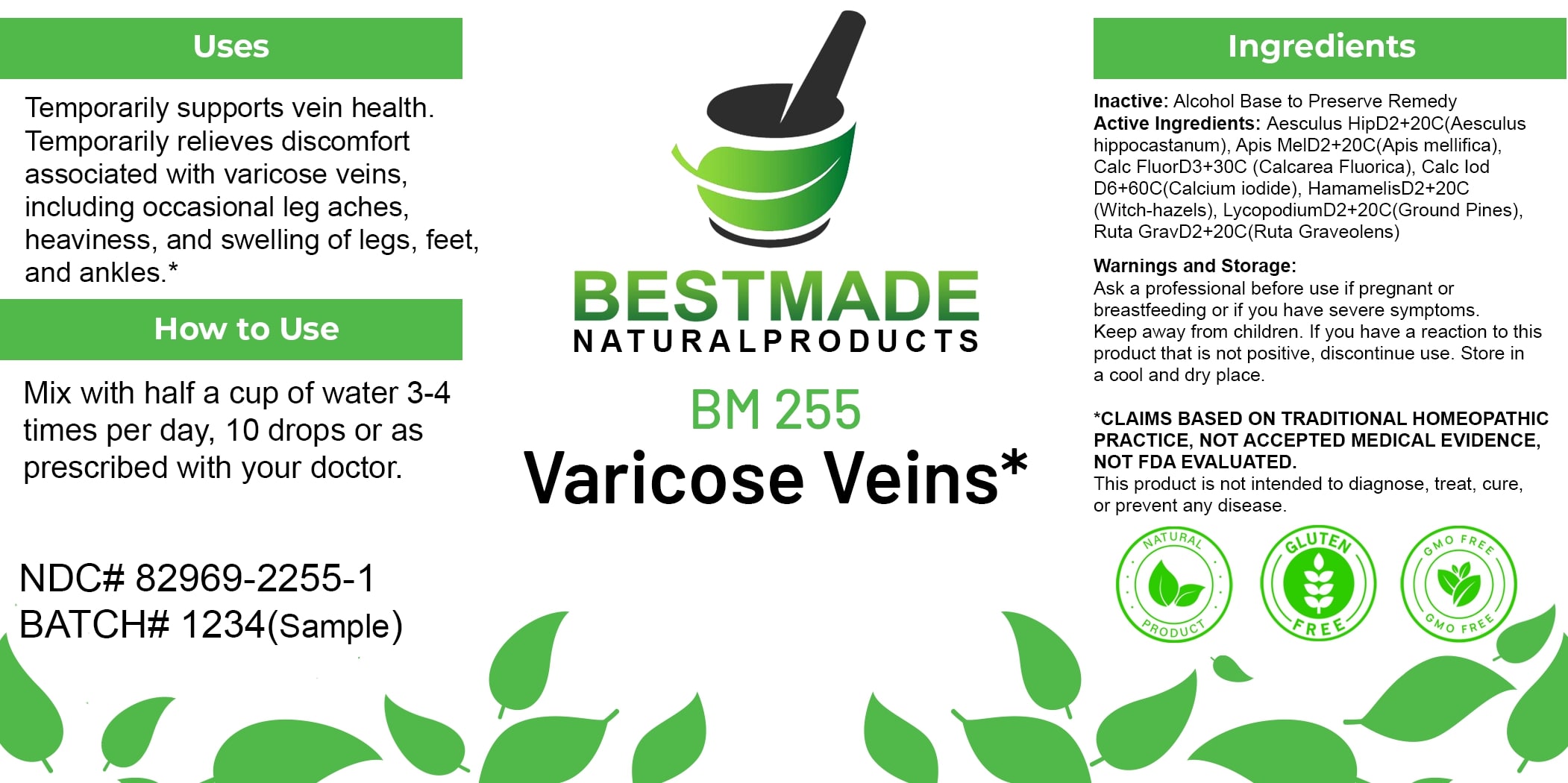 DRUG LABEL: Bestmade Natural Products BM255
NDC: 82969-2255 | Form: LIQUID
Manufacturer: Bestmade Natural Products
Category: homeopathic | Type: HUMAN OTC DRUG LABEL
Date: 20250306

ACTIVE INGREDIENTS: APIS MELLIFERA 30 [hp_C]/30 [hp_C]; CALCIUM FLUORIDE 30 [hp_C]/30 [hp_C]; LYCOPODIUM CLAVATUM SPORE 30 [hp_C]/30 [hp_C]; HAMAMELIS VIRGINIANA ROOT BARK/STEM BARK 30 [hp_C]/30 [hp_C]; CALCIUM IODIDE 30 [hp_C]/30 [hp_C]; HORSE CHESTNUT 30 [hp_C]/30 [hp_C]; RUTA GRAVEOLENS FLOWERING TOP 30 [hp_C]/30 [hp_C]
INACTIVE INGREDIENTS: ALCOHOL 30 [hp_C]/30 [hp_C]

BM255

DOSAGE AND ADMINISTRATION

How to Use

Mix with half a cup of water 3-4 times per day, 10 drops or as prescribed with your doctor.

Uses

Temporarily supports vein health. Temporarily relieves discomfort associated with varicose veins, including occasional leg aches, heaviness, and swelling of legs, feet, and ankles.*

*CLAIMS BASED ON TRADITIONAL HOMEOPATHIC PRACTICE, NOT ACCEPTED MEDICAL EVIDENCE. NOT FDA EVALUATED.

This product is not intended to diagnose, treat, cure, or prevent any disease.

INACTIVE INGREDIENT

Ingredients

Inactive: Alcohol Base to Preserve Remedy

ACTIVE INGREDIENT

Active Ingredients: Aesculus HipD2+20C(Aesculus Hippocastanum), Apis MellD2+20C(Apis mellifica), Calc FluorD3+30C(Calcarea Fluorica), Calc Iod D6+60C(Calcium Iodide), HamamelisD2+20C (Witch-hazels), LycopodiumD2+20C(Ground Pines), Ruta GravD2+20C(Ruta Graveolens)

KEEP OUT OF REACH OF CHILDREN

Warnings and Storage:

Ask a professional before use if pregnant or breastfeeding or if you have severe symptoms. Keep away from children. If you have a reaction to this product that is not positive, discontinue use. Store in a cool and dry place.

Warnings and Storage:

Ask a professional before use if pregnant or breastfeeding or if you have severe symptoms. Keep away from children. If you have a reaction to this product that is not positive, discontinue use. Store in a cool and dry place.

*CLAIMS BASED ON TRADITIONAL HOMEOPATHIC PRACTICE, NOT ACCEPTED MEDICAL EVIDENCE. NOT FDA EVALUATED.

This product is not intended to diagnose, treat, cure, or prevent any disease.

Uses

Temporarily supports vein health. Temporarily relieves discomfort associated with varicose veins, including occasional leg aches, heaviness, and swelling of legs, feet, and ankles.*

*CLAIMS BASED ON TRADITIONAL HOMEOPATHIC PRACTICE, NOT ACCEPTED MEDICAL EVIDENCE. NOT FDA EVALUATED.

This product is not intended to diagnose, treat, cure, or prevent any disease.

Entire package label